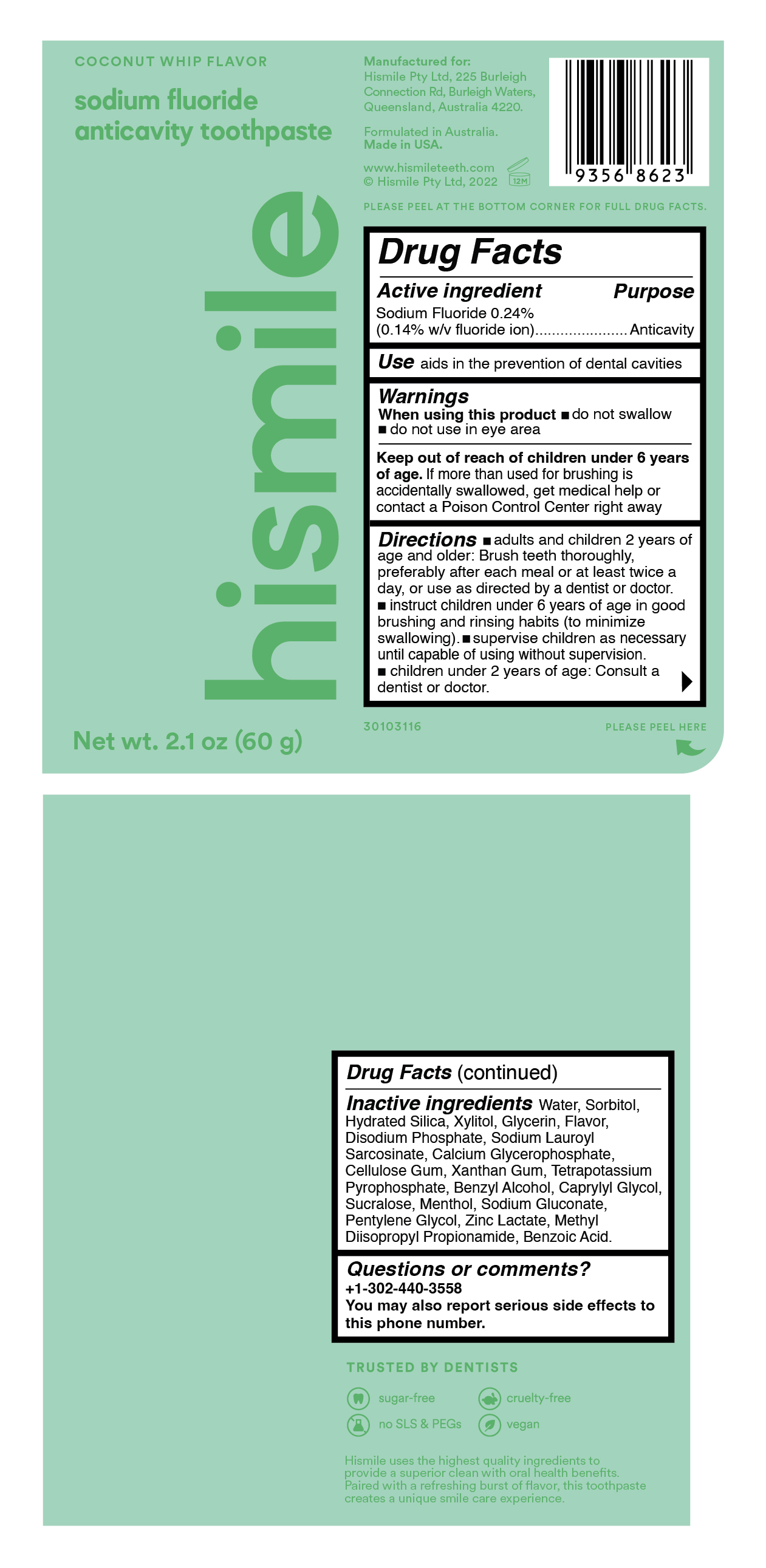 DRUG LABEL: Hismile
NDC: 83013-312 | Form: GEL
Manufacturer: Hismile Pty Ltd
Category: otc | Type: HUMAN OTC DRUG LABEL
Date: 20260115

ACTIVE INGREDIENTS: SODIUM FLUORIDE 2.4 mg/1 g
INACTIVE INGREDIENTS: CARBOXYMETHYLCELLULOSE SODIUM, UNSPECIFIED FORM; SODIUM GLUCONATE; PENTYLENE GLYCOL; METHYL DIISOPROPYL PROPIONAMIDE; BENZOIC ACID; SODIUM PHOSPHATE, DIBASIC, ANHYDROUS; SORBITOL; POTASSIUM PYROPHOSPHATE; SODIUM LAUROYL SARCOSINATE; GLYCERIN; BENZYL ALCOHOL; SUCRALOSE; MENTHOL; ZINC LACTATE; CAPRYLYL GLYCOL; WATER; CALCIUM GLYCEROPHOSPHATE; XANTHAN GUM; HYDRATED SILICA; XYLITOL

Coconut Whip Flavor Sodium Fluoride Anticavity Toothpaste

Active ingredient

Sodium Fluoride 0.24% (0.14% w/v fluoride ion)

Purpose

Anticavity

Use

aids in the prevention of dental cavities

Warnings

When using this product

- do not swallow
- do not use in eye area

Keep out of reach of children under 6 years of age

If more than used for brushing is accidentally swallowed, get medical help or contact a Poison Control Center right away

Directions

- adults and children 2 years of age and older: Brush teeth thoroughly, preferably after each meal or at least twice a day, or use as directed by a dentist or doctor.
- instruct children under 6 years of age in good brushing and rinsing habits (to minimize swallowing.)
- supervise children as neceaasry until capable of using without supervision.
- children under 2 years of age: Consult a dentist or doctor.

Inactive ingredients

Water, Sorbitol, Hydrated Silica, Xylitol, Glycerin, Flavor, Disodium Phosphate, Sodium Lauroyl Sarcosinate, Calcium Glycerophosphate, Xanthan Gum, Cellulose Gum, Tetrapotassium Pyrophosphate, Benzyl Alcohol, Caprylyl Glycol, Sucralose, Menthol, Sodium Gluconate, Pentylene Glycol, Zinc Lactate, Methyl Diisopropyl Propionamide, Benzoic Acid

label

Coconut Whip Flavor Sodium Fluoride Anticavity Toothpaste

Manufactured for:
Hismile Pty Ltd, 225 Burleigh
Connection Rd, Burleigh Waters,
Queensland, Australia 4220.

Formulated in Australia.
Made in USA.

www.hismileteeth.com
© Hismile Pty Ltd, 2022

TRUSTED BY DENTISTS

sugar-free
cruelty- free
no SLS & PEGs
vegan

Hismile uses the highest quality ingredients to provide a superior clean with oral health benefits. Paired with a refreshing burst of flavor, this toothpaste creates a unique smile care experience.